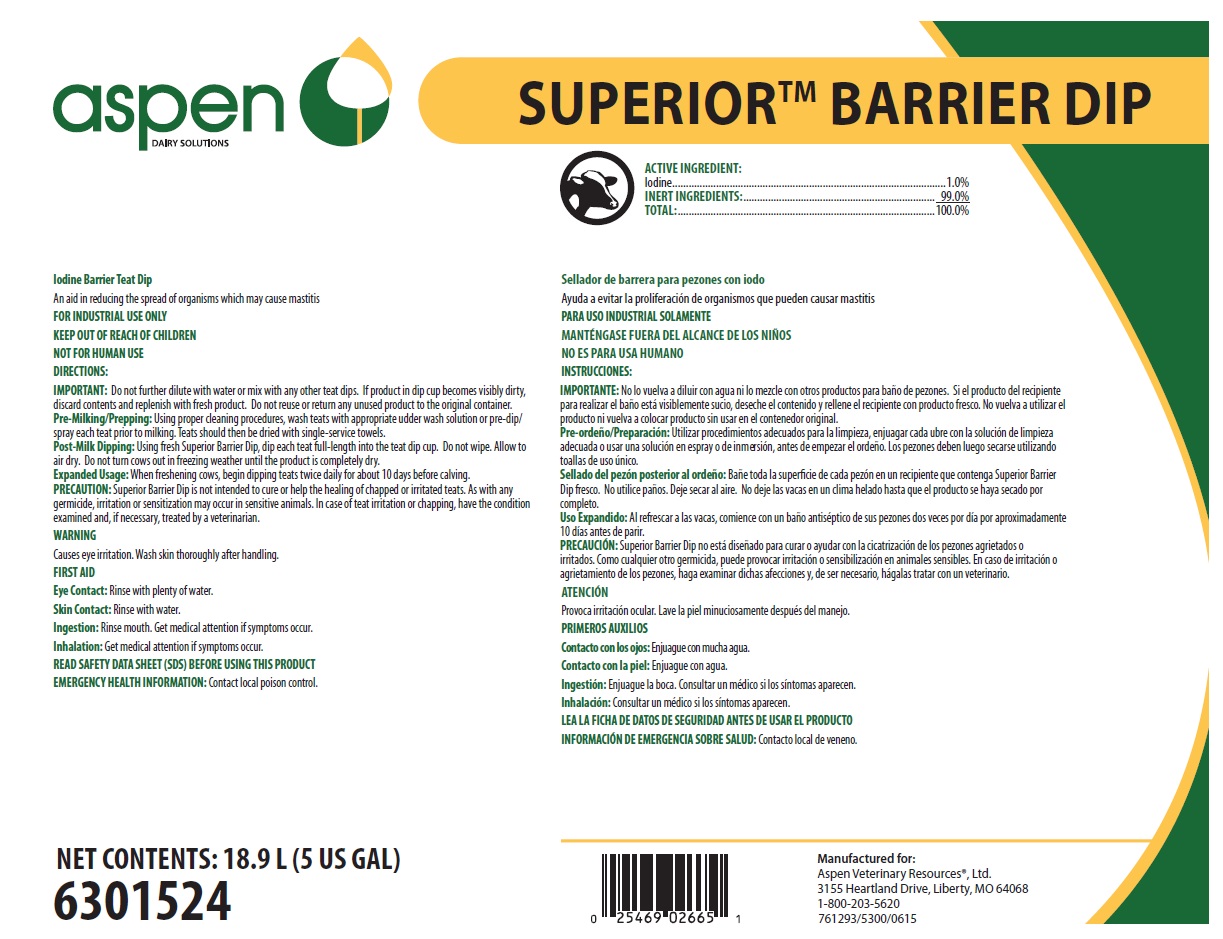 DRUG LABEL: Aspen
NDC: 46066-407 | Form: SOLUTION
Manufacturer: Animal Health International
Category: animal | Type: OTC ANIMAL DRUG LABEL
Date: 20200203

ACTIVE INGREDIENTS: IODINE 10 mg/1 mL
INACTIVE INGREDIENTS: WATER

SAFE HANDLING WARNING

FOR INDUSTRIAL USE ONLY

KEEP OUT OF REACH OF CHILDREN

NOT FOR HUMAN USE

WARNING

Causes eye irritation. Wash skin thoroughly after handling.

DIRECTIONS:

IMPORTANT: Do not further dilute with water or mix with any other teat dips. If product in dip cup becomes visibly dirty, discard contents and replenish with fresh product. Do not reuse or return any unused product to the original container.

Pre-Milking/Prepping: Using proper cleaning procedures, wash teats with appropriate udder wash solution or pre-dip/spray each teat prior to milking. Teats should then be dried with single-service towels.

Post-Milk Dipping: Using fresh Superior Barrier Dip, dip each teat full-length into the teat dip cup. Do not wipe. Allow to air dry. Do not turn cows out in freezing weather until the product is completely dry.

Expanded Usage: When freshening cows, begin dipping teats twice daily for about 10 days before calving.

PRECAUTION: Superior Barrier Dip is not intended to cure or help the healing of chapped or irritated teats. As with any germicide, irritation or sensitization may occur in sensitive animals. In case of teat irritation or chapping, have the condition examined and, if necessary, treated by a veterinarian.

OTHER SAFETY INFORMATION

FIRST AID

Eye Contact: Rinse with plenty of water.

Skin Contact: Rinse with water.

Ingestion: Rinse mouth. Get medical attention if symptoms occur.

Inhalation: Get medical attention if symptoms occur.

READ SAFETY DATA SHEET (SDS) BEFORE USING THIS PRODUCT

EMERGENCY HEALTH INFORMATION: Contact local poison control.

Representative label and principal display panel

Aspen DAIRY SOLUTIONS

SUPERIORTM BARRIER DIP

ACTIVE INGREDIENT:

Iodine.....................................................................................................1.0%

INERT INGREDIENTS:....................................................................... 99.0%

TOTAL:...............................................................................................100.0%

Iodine Barrier Teat Dip

An aid in reducing the spread of organisms which may cause mastitis

NET CONTENTS: 18.9 L (5 US GAL)

6301526

Manufactured for:

Aspen Veterinary Resources®, Ltd.

3155 Heartland Drive, Liberty, MO 64068

1-800-203-5620

76129/5300/0615